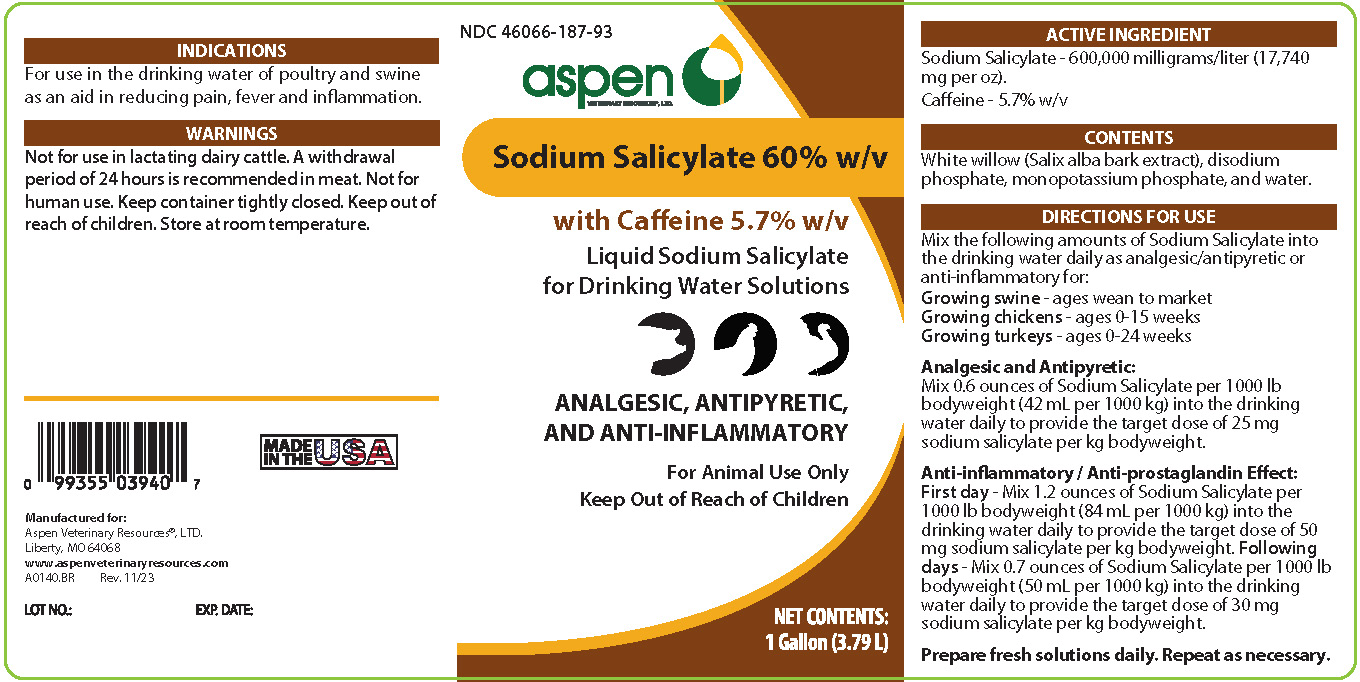 DRUG LABEL: Aspen Sodium Salicylate 60% with Caffeine 5.7%
NDC: 46066-187 | Form: LIQUID
Manufacturer: Aspen Veterinary Resources, Ltd.
Category: animal | Type: OTC ANIMAL DRUG LABEL
Date: 20231229

ACTIVE INGREDIENTS: SODIUM SALICYLATE 600 g/1 L; CAFFEINE 57 g/1 L

Aspen Sodium Salicylate 60% with Caffeine 5.7%

INDICATIONS

For use in the drinking water of poultry and swine as an aid in reducing pain, fever and inflammation.

WARNINGS

Not for use in lactating dairy cattle. A withdrawal period of 24 hours is recommended in meat. Not for human use. Keep container tightly closed. Keep out of reach of children. Store at room temperature.

DIRECTIONS FOR USE

Mix the following amounts of Sodium Salicylate into the drinking water daily as analgesic/antipyretic or anti-inflammatory for:

Growing swine - ages wean to market

Growing Chickens - ages 0-15 weeks

Growing turkeys - ages 0-24 weeks

Analgesic and Antipyretic:

Mix 0.6 ounces of Sodium Salicylate per 1000 lb bodyweight (42 mL per 1000 kg) into the drinking water daily to provide the target dose of 25 mg sodium salicylate per kg bodyweight.

Anti-inflammatory / Anti-prostaglandin Effect:

First day - Mix 1.2 ounces of Sodium Salicylate per 1000 lb bodyweight (84 mL per 1000 kg) into the drinking water daily to provide the target dose of 50 mg sodium salicylate per kg bodyweight.

Following days - Mix 0.7 ounces of Sodium Salicylate per 1000 lb bodyweight (50 mL per 1000 kg) into the drinking water daily to provide the target dose of 30 mg sodium salicylate per kg bodyweight.

Prepare fresh solutions daily. Repeat as necessary.

PACKAGE LABEL

Add image transcription here...